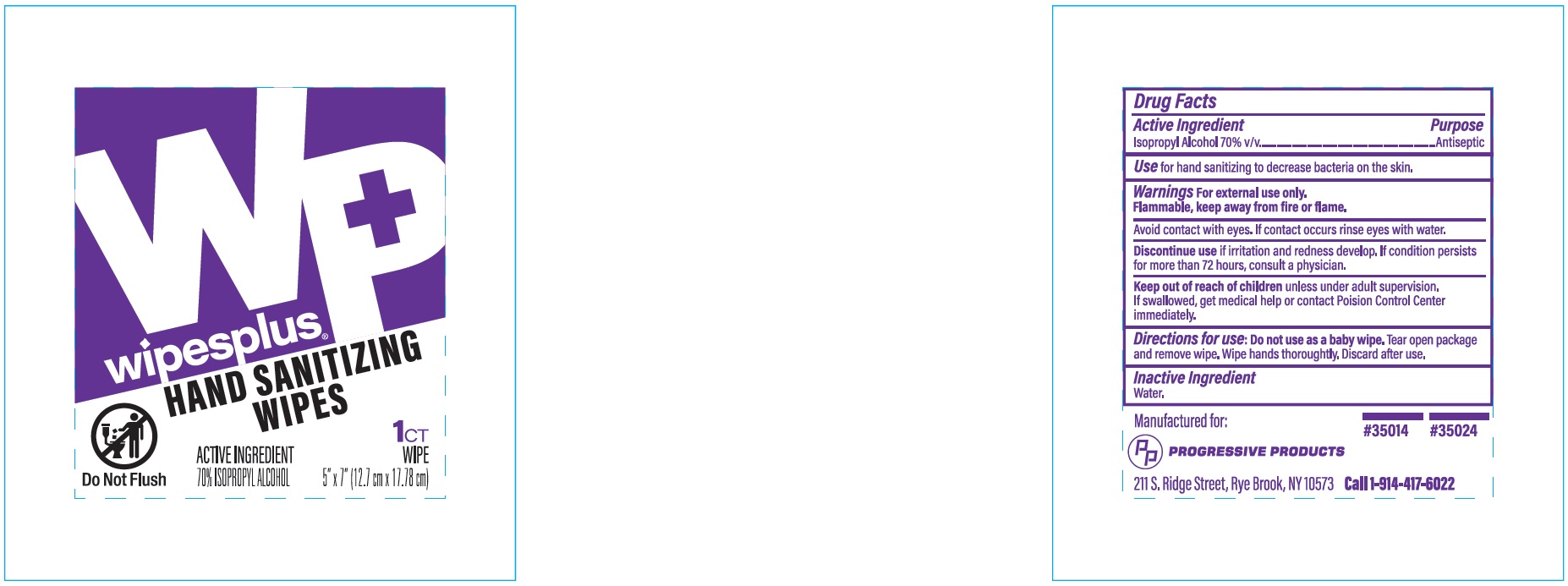 DRUG LABEL: Wipesplus Hand Sanitizing Wipes
NDC: 67151-727 | Form: CLOTH
Manufacturer: Progressive Products, LLC
Category: otc | Type: HUMAN OTC DRUG LABEL
Date: 20221014

ACTIVE INGREDIENTS: ISOPROPYL ALCOHOL 0.7 mL/1 1
INACTIVE INGREDIENTS: WATER

Drug Facts

Active Ingredient

Isopropyl Alcohol 70% v/v

Purpose

Antiseptic

Use

for hand sanitizing to decrease bacteria on the skin.

Warnings

For external use only.

Flammable, keep away from fire or flame.

Warnings

Avoid contact with eyes. If contact occurs rinse eyes with water.

Discontinue use

if irritation and redness develop. If condition persists for more than 72 hours, consult a physician.

Keep out of reach of children

unless under adult supervision. If swallowed, get medical help or contact Posion Control Center immediately.

Directions for use

Do not use as a baby wipe. Tear open package and remover wipe. Wipe hands thoroughly. Discard after use.

Inactive Ingredient

Water

Principal Display Panel

wipesplus

HAND SANITIZING WIPES

1CT WIPE